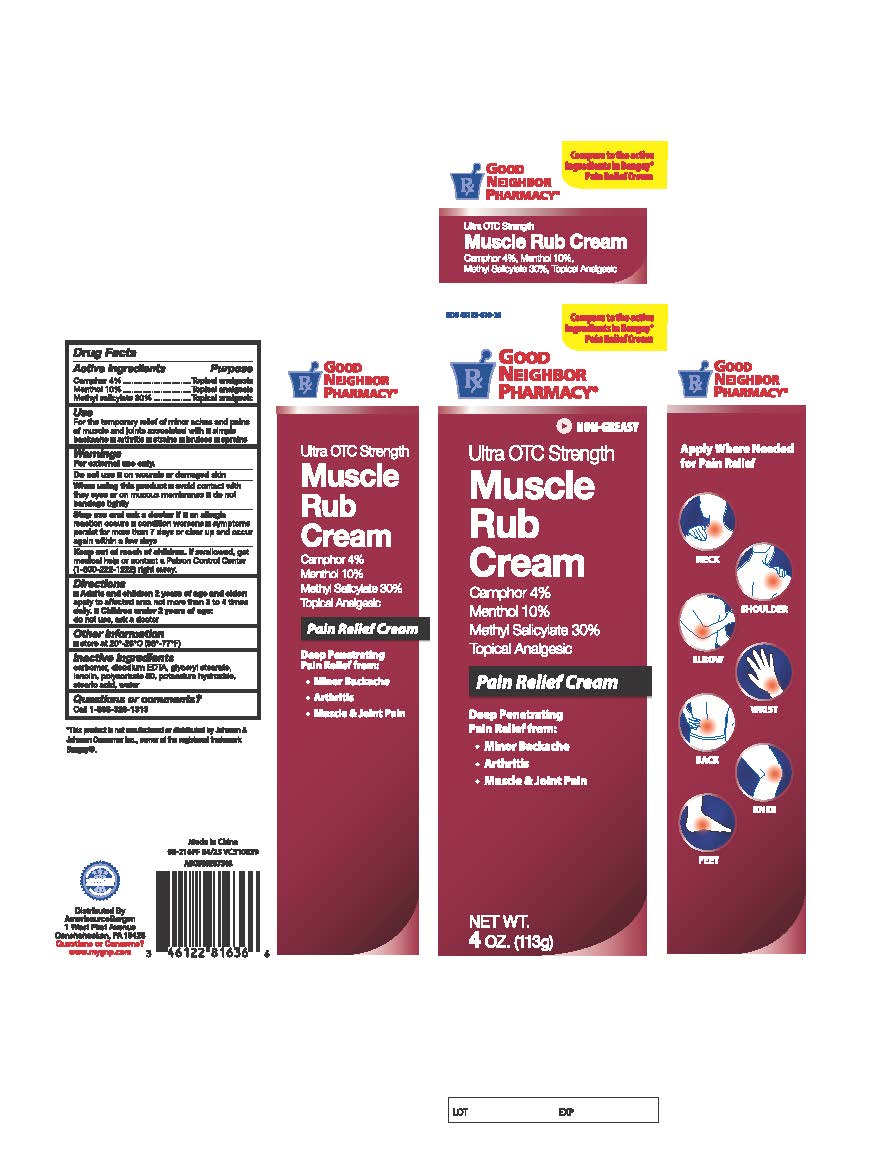 DRUG LABEL: Good Neighbor Muscle Rub Cream
NDC: 46122-816 | Form: CREAM
Manufacturer: Amerisource Bergen
Category: otc | Type: HUMAN OTC DRUG LABEL
Date: 20250507

ACTIVE INGREDIENTS: MENTHOL, UNSPECIFIED FORM 100 mg/1 g; CAMPHOR (SYNTHETIC) 40 mg/1 g; METHYL SALICYLATE 300 mg/1 g
INACTIVE INGREDIENTS: EDETATE DISODIUM ANHYDROUS; STEARIC ACID; LANOLIN; POLYSORBATE 80; GLYCERYL 1-STEARATE; CARBOMER INTERPOLYMER TYPE A (55000 CPS); WATER; POTASSIUM HYDROXIDE

Good Neighbor Muscle Rub Cream

Active Ingredient

Camphor 4%

Menthol 10%

Methyl salicylate 30%

Purpose

Topical Analgesic

Topical Analgesic

Topical Analgesic

Use

temporarily relieves the minor aches and pains of muscles and joints associated with:

- simple backache
- arthritis
- strains
- bruises
- sprains

Warnings

For external use only.

Do not Use

- on wounds or damaged skin

When Using Section

- avoid contact with eyes or mucous membranes
- do not bandage tightly

Stop use and ask a doctor if

- an allergic reaction occurs
- condition worsens
- symptoms last more than 7 days or clear up and occur again within a few days

Keep out of reach of children

If swallowed, get medical help or contact a Poison Control Center (1-800-222-1222) right away.

Directions

- adults and children 2 years of age and older: apply to affected area not more than 3 to 4 times daily
- children under 2 years of age: do not use, ask a doctor

Other Information

- store at 20° to 25°C (68° to 77°F)

Inactive Ingredients

carbomer, disodium ESTA, glyceryl stearate, lanolin, polysorbate 80, potassium hydroxide, stearic acid, water.

Questions

Call 1-866-326-1313